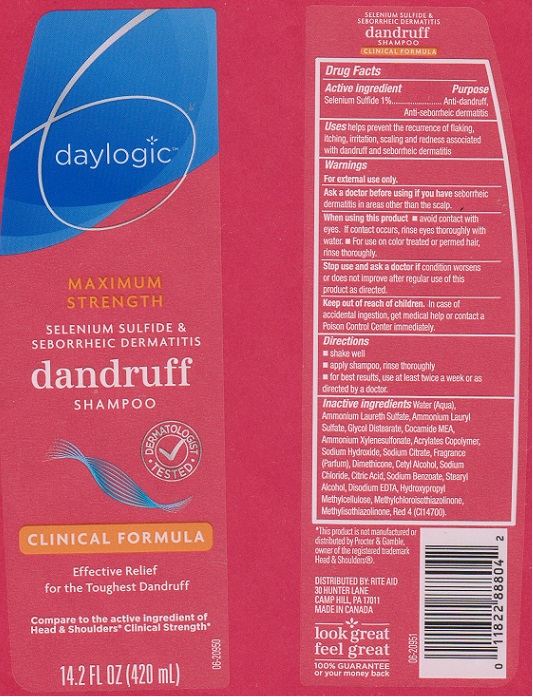 DRUG LABEL: Daylogic Maximum Strength Dandruff
NDC: 11822-6181 | Form: LIQUID
Manufacturer: RITE AID CORPORATION
Category: otc | Type: HUMAN OTC DRUG LABEL
Date: 20160210

ACTIVE INGREDIENTS: SELENIUM SULFIDE 10 mg/1 mL
INACTIVE INGREDIENTS: WATER; AMMONIUM LAURETH-3 SULFATE; AMMONIUM LAURYL SULFATE; GLYCOL DISTEARATE; COCO MONOETHANOLAMIDE; AMMONIUM XYLENESULFONATE; METHACRYLIC ACID - METHYL METHACRYLATE COPOLYMER (1:1); SODIUM HYDROXIDE; SODIUM CITRATE; DIMETHICONE; CETYL ALCOHOL; SODIUM CHLORIDE; CITRIC ACID MONOHYDRATE; SODIUM BENZOATE; STEARYL ALCOHOL; EDETATE DISODIUM; HYPROMELLOSES; METHYLCHLOROISOTHIAZOLINONE; METHYLISOTHIAZOLINONE; FD&C RED NO. 4

DRUG FACTS

Active ingredient

Selenium Sulfide 1%

Purpose

Anti-dandruff, Anti-seborrheic dermatitis

Uses

helps prevent the recurrence of flaking, itching, irritation, scaling and redness associated with dandruff and seborrheic dermatitis.

Warnings

For external use only.

Ask a doctor before using if you have

seborrheic dermatitis in areas other than the scalp.

Stop use and ask a doctor if

condition worsens or does not improve after regular use of this product as directed.

Keep out of reach of children.

In case of accidental ingestion, get medical help or contact a Poison Control Center immediately.

Directions

- shake well
- apply shampoo, rinse thoroughly
- for best results, use at least twice a week or as directed by a doctor

Inactive ingredients

Water (Aqua), Ammonium Laureth Sulfate, Ammonium Lauryl Sulfate, Glycol Distearate, Cocamide MEA, Ammonium Xylenesulfonate, Acrylates Copolymer, Sodium Hydroxide, Sodium Citrate, Fragrance (Parfum), Dimethicone, Cetyl Alcohol, Sodium Chloride, Citric Acid, Sodium Benzoate, Stearyl Alcohol, Disodium EDTA, Hydroxypropyl Methylcellulose, Methylchloroisothiazolinone, Methylisothiazolinone, Red 4 (CI 14700).